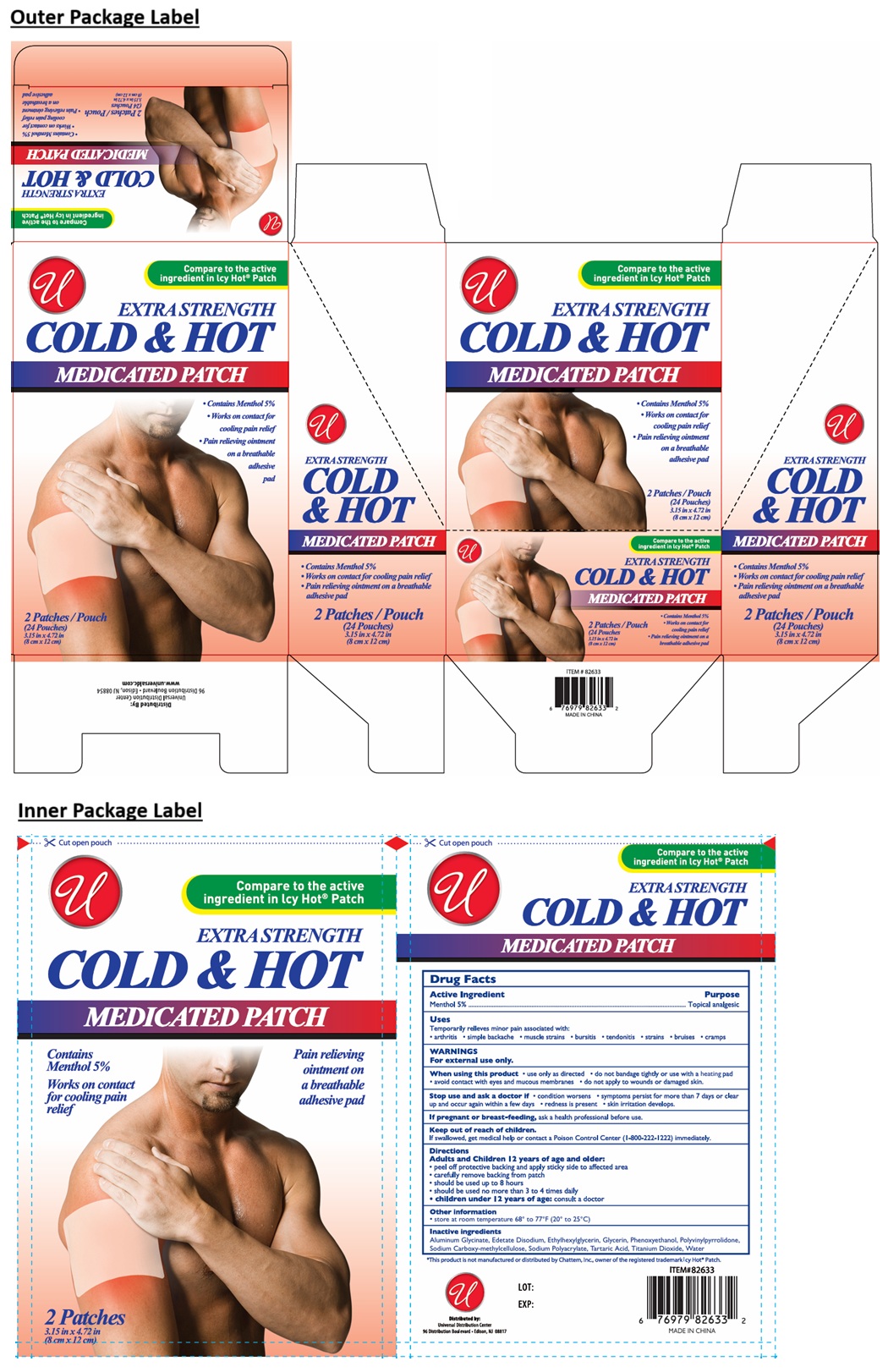 DRUG LABEL: COLD AND HOT MEDICATED
NDC: 52000-422 | Form: PATCH
Manufacturer: Universal Distribution Center LLC
Category: otc | Type: HUMAN OTC DRUG LABEL
Date: 20250929

ACTIVE INGREDIENTS: MENTHOL, UNSPECIFIED FORM 0.05 g/1 g
INACTIVE INGREDIENTS: DIHYDROXYALUMINUM AMINOACETATE ANHYDROUS; EDETATE DISODIUM; ETHYLHEXYLGLYCERIN; GLYCERIN; PHENOXYETHANOL; POVIDONE, UNSPECIFIED; CARBOXYMETHYLCELLULOSE SODIUM, UNSPECIFIED; SODIUM POLYACRYLATE (2500000 MW); TARTARIC ACID; TITANIUM DIOXIDE; WATER

COLD AND HOT MEDICATED PATCH

Active Ingredient

Menthol 5%

Purpose

Topical analgesic

Uses

Temporarily relieve minor pain associated with:
• arthritis • simple backache • muscle strains • bursitis • tendonitis • strains • bruises • cramps

WARNINGS

For external use only.

When using this product • use only as directed • do not bandage tightly or use with a heating pad
• avoid contact with eyes and mucous membranes • do not apply to wounds or damaged skin.

Stop use and ask a doctor if • condition worsens • symptoms persist for more than 7 days or clear up and occur again within a few days • redness is present • skin irritation develops.

If pregnant or breast-feeding, ask a health professional before use.

Keep out of reach of children.
If swallowed, get medical help or contact a Poison Control Center (1-800-222-1222) immediately.

Directions

Adults and Children 12 years of age and older:
• peel off protective backing and apply sticky side to affected area
• carefully remove backing from patch
• should be used up to 8 hours
• should be used no more than 3 to 4 times daily
• children under 12 years of age: consult a doctor

Other Information

• store at room temperature 68° to 77°F (20° to 25°C)

Inactive Ingredients

Aluminum Glycinate, Edetate Disodium, Ethylhexylglycerin, Glycerin, Phenoxyethanol, Polyvinylpyrrolidone, Sodium Carboxy-methylcellulose, Sodium Polyacrylate, Tartaric Acid, Titanium Dioxide, Water

Compare to the active ingredient in Icy Hot® Patch

EXTRA STRENGTH

Contains Menthol 5%

Works on contact for cooling pain relief

Pain relieving ointment on a breathable adhesive pad

*This product is not manufactured or distributed by Chattem Inc., owner of the registered trademark Icy Hot® Patch.

Distributed by:

Universal Distribution Center
96 Distribution Boulevard • Edison, NJ 08817

MADE IN CHINA

www.universaldc.com